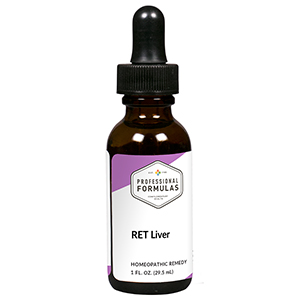 DRUG LABEL: RET Liver
NDC: 63083-7008 | Form: LIQUID
Manufacturer: Professional Complementary Health Formulas
Category: homeopathic | Type: HUMAN OTC DRUG LABEL
Date: 20190815

ACTIVE INGREDIENTS: CICHORIUM INTYBUS FLOWER 3 [hp_X]/29.5 mL; VERBENA OFFICINALIS FLOWERING TOP 3 [hp_X]/29.5 mL; SODIUM PHOSPHATE, DIBASIC, HEPTAHYDRATE 3 [hp_X]/29.5 mL; SODIUM CHLORIDE 3 [hp_X]/29.5 mL; ACONITUM NAPELLUS WHOLE 30 [hp_X]/29.5 mL; ANACARDIUM OCCIDENTALE BARK 30 [hp_X]/29.5 mL; GOLD 30 [hp_X]/29.5 mL; CALCIUM SULFIDE 30 [hp_X]/29.5 mL; POTASSIUM CARBONATE 30 [hp_X]/29.5 mL; NITRIC ACID 30 [hp_X]/29.5 mL; STRYCHNOS NUX-VOMICA SEED 30 [hp_X]/29.5 mL; DELPHINIUM STAPHISAGRIA SEED 30 [hp_X]/29.5 mL
INACTIVE INGREDIENTS: ALCOHOL; WATER

RET8

ACTIVE INGREDIENTS

Chicory flower essence 3X
Vervain flower essence 3X
Nat phos 3X, 6X, 30X
Nat mur 3X, 6X, 30X, 100X, 200X
and all the following at 30X, 100X, 200X:
Aconitum nap
Anacardium
Aur met
Hepar sulph calc
Kali carb
Nitricum ac
Nux vom
Staphysag

QUESTIONS

Professional Formulas

PO Box 2034 Lake Oswego, OR 97035

INDICATIONS

Temporarily relieves anger, aggravation, irritability, overenthusiasm, hyperactivity, being overly possessive, protective, critical, manipulating, or demanding, or being easily offended.*

PURPOSE

*Claims based on traditional homeopathic practice, not accepted medical evidence. Not FDA evaluated.

WARNINGS

In case of overdose, get medical help or contact a poison control center right away.

Keep out of the reach of children.

PREGNANCY OR BREAST FEEDING

If pregnant or breastfeeding, ask a healthcare professional before use.

DIRECTIONS

Place drops under tongue 30 minutes before/after meals. Adults and children 12 years and over: Take 5 drops up to 4 times per day for up to one month. Consult a physician for use in children under 12 years of age.

OTHER INFORMATION

Tamper resistant. If seal is broken, do not use. After opening, close container tightly and store at room temperature away from heat.

INACTIVE INGREDIENTS

20% ethanol, purified water.

LABEL

Est 1985

Professional Formulas

Complementary Health

RET Liver

Homeopathic Remedy

1 FL. OZ. (29.5 mL)